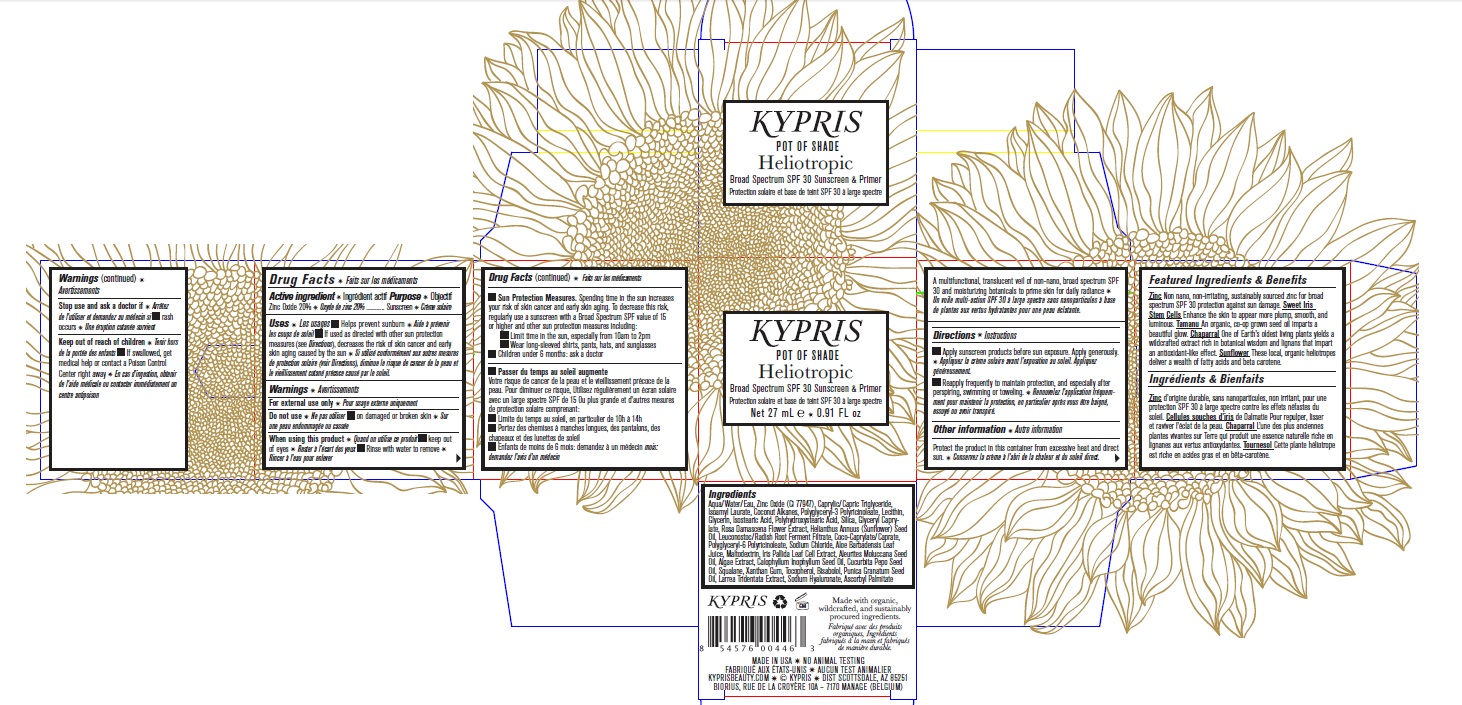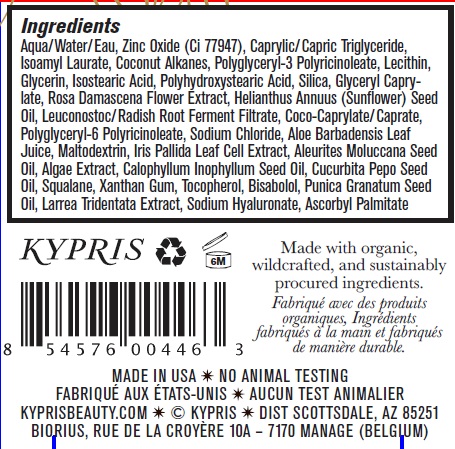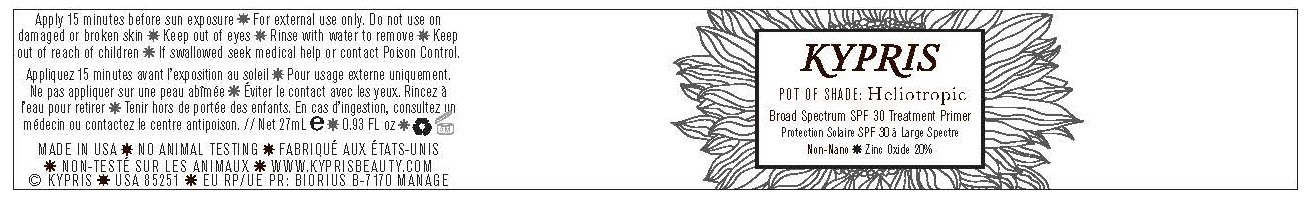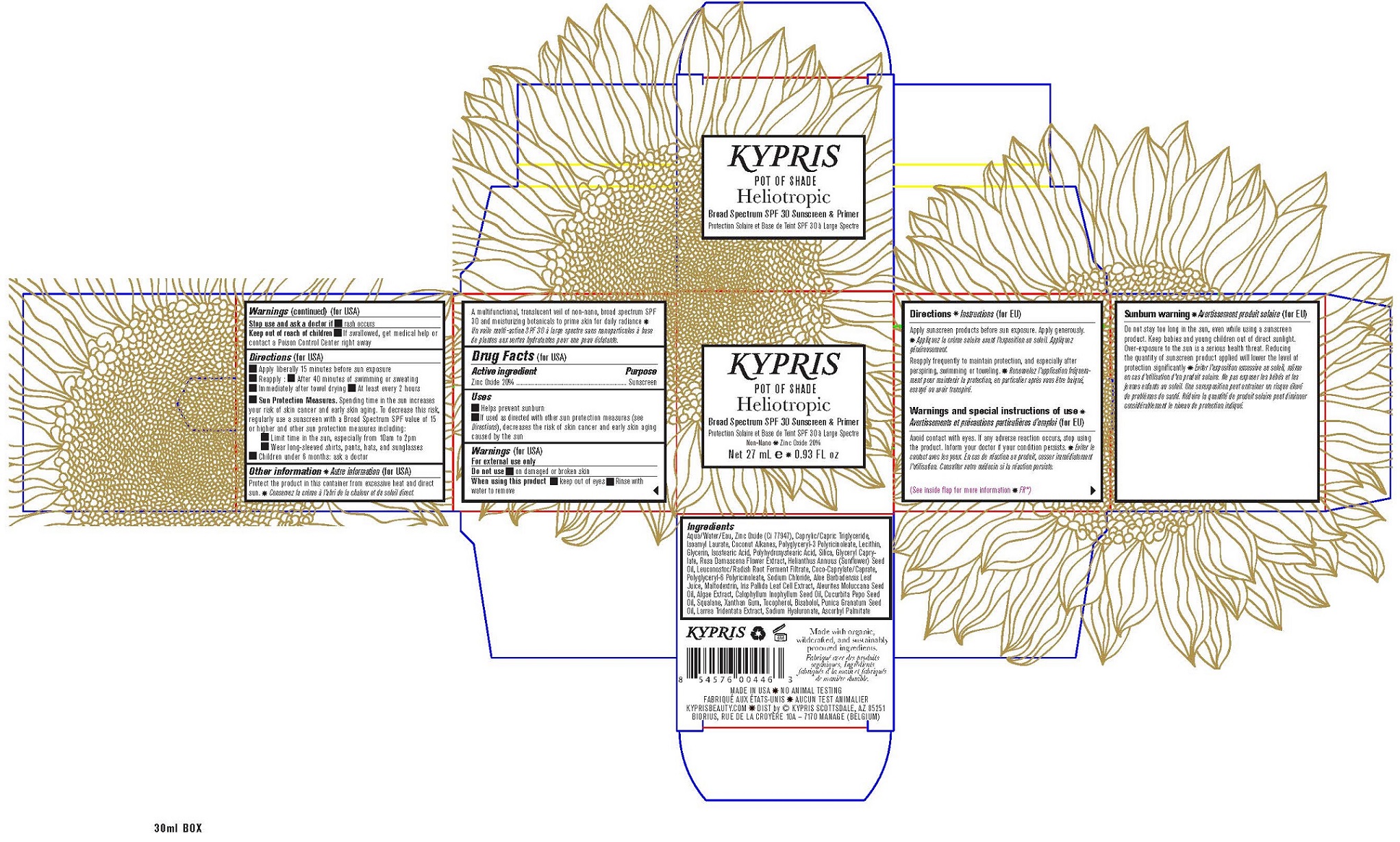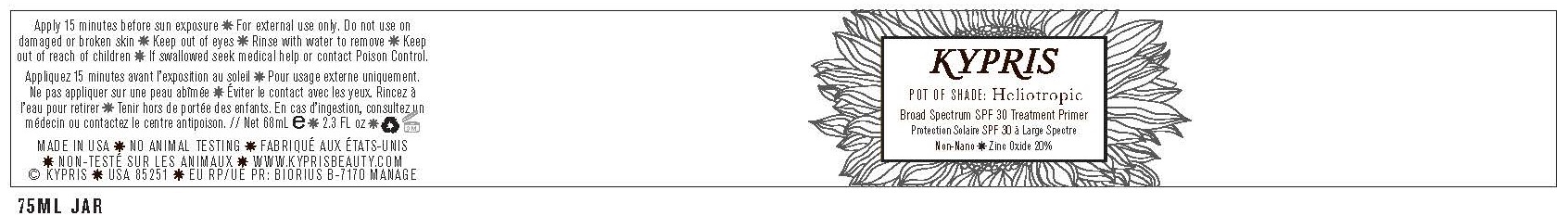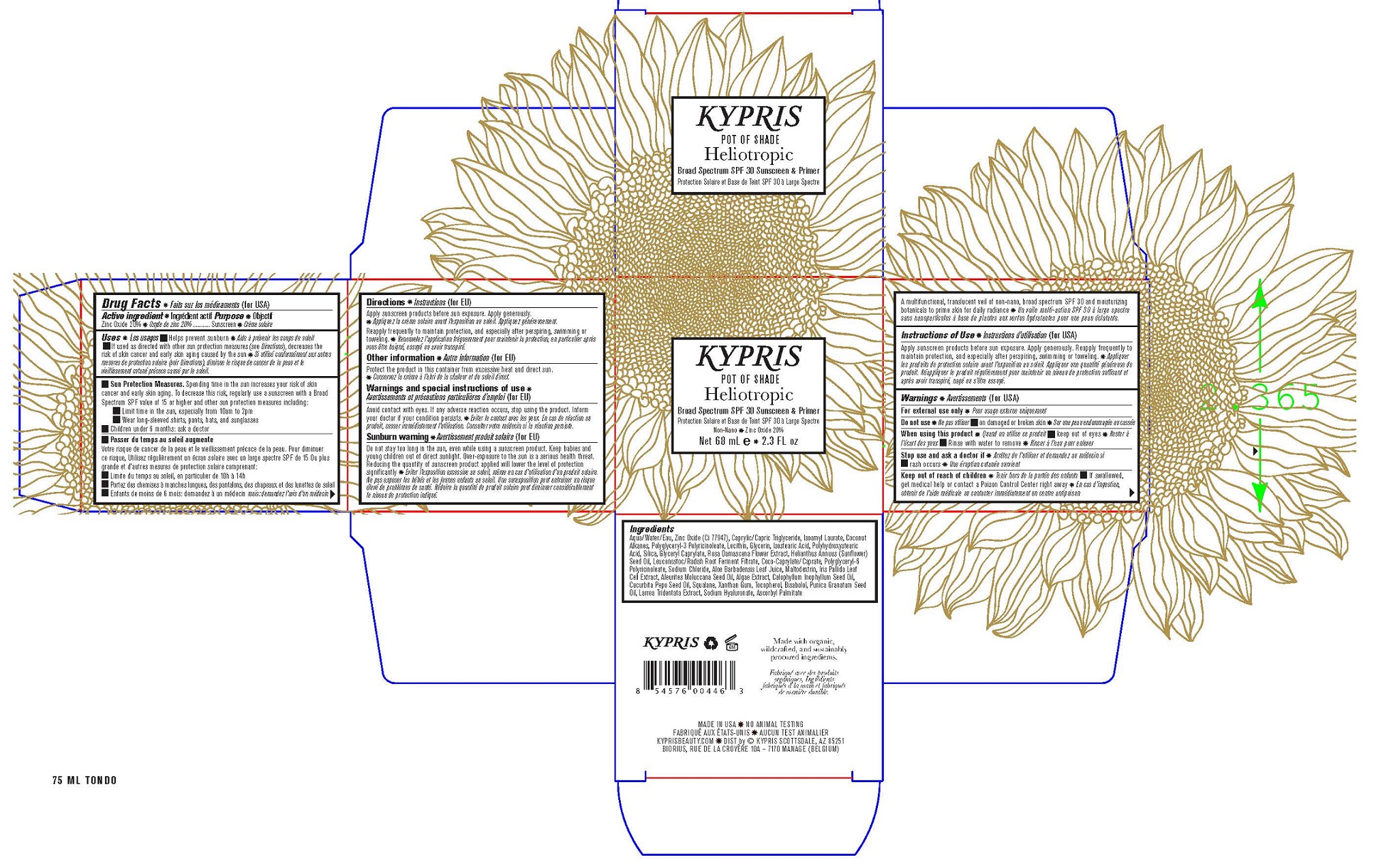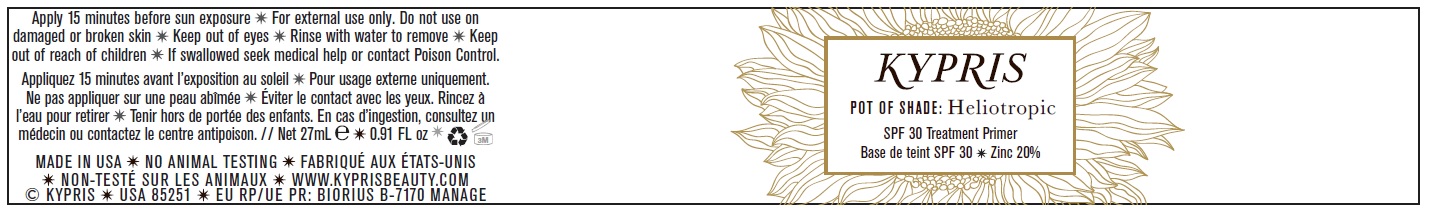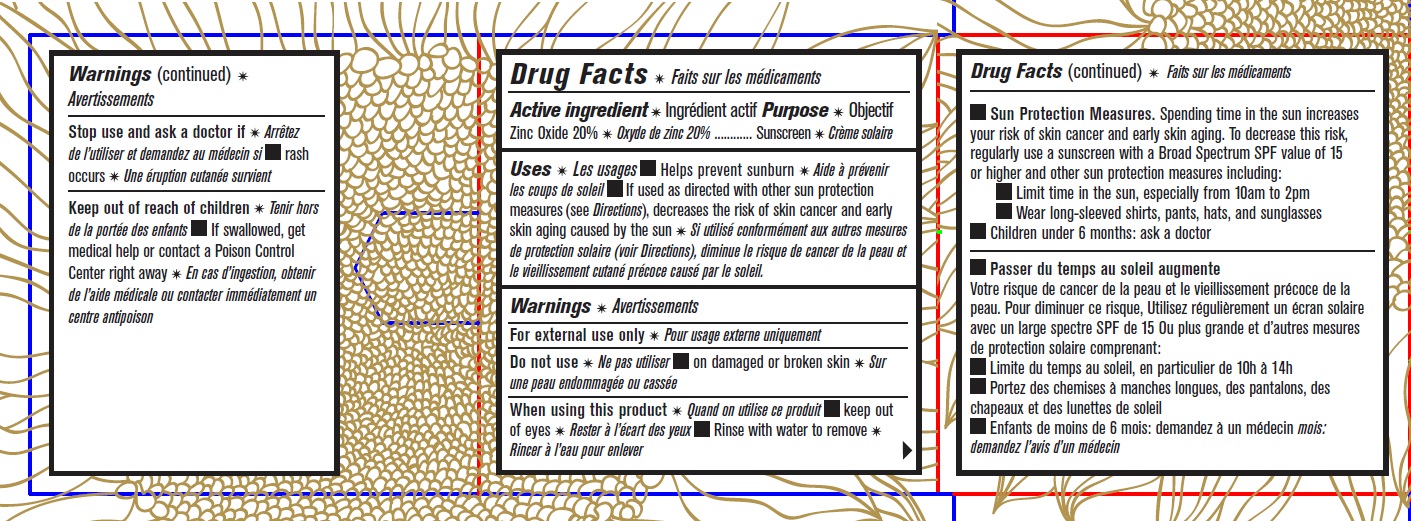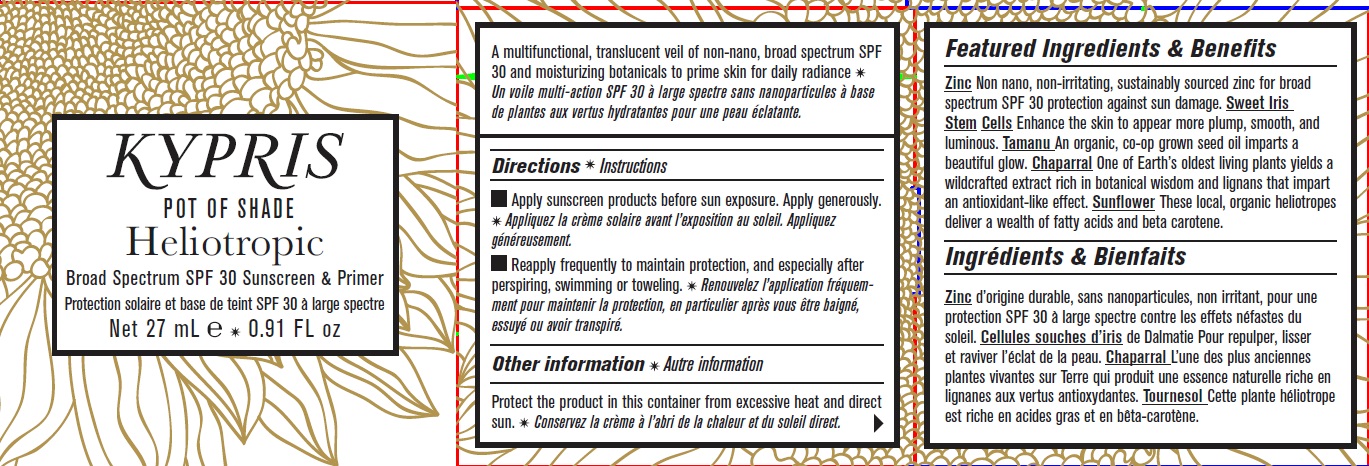 DRUG LABEL: Kypris Pot of Shade Heliotropic Broad Spectrum SPF 30 Sunscreen And Primer
NDC: 70608-001 | Form: CREAM
Manufacturer: Kypris Beauty LLC
Category: otc | Type: HUMAN OTC DRUG LABEL
Date: 20260227

ACTIVE INGREDIENTS: ZINC OXIDE 200 mg/1 mL
INACTIVE INGREDIENTS: WATER; MEDIUM-CHAIN TRIGLYCERIDES; ISOAMYL LAURATE; COCONUT ALKANES; GLYCERIN; SILICON DIOXIDE; GLYCERYL CAPRYLATE; ROSA X DAMASCENA FLOWER; ALOE VERA LEAF; ISOSTEARIC ACID; SUNFLOWER OIL; SODIUM CHLORIDE; COCO-CAPRYLATE/CAPRATE; KUKUI NUT; PUMPKIN SEED OIL; SQUALANE; XANTHAN GUM; TAMANU OIL; POMEGRANATE; LEVOMENOL; TOCOPHEROL; HYALURONATE SODIUM; CITRIC ACID MONOHYDRATE

Kypris Pot of Shade Heliotropic Broad Spectrum SPF 30 Sunscreen & Primer

Active ingredient

Zinc Oxide 20%

Purpose

Sunscreen

Uses

- Helps prevent sunburn
- If used as directed with other sun protection measures (see Directions), decreases the risk of skin cancer and early skin aging caused by the sun.

Warnings

For external use only

Do not use

- on damaged or broken skin

When using this product

- keep out of eyes
- Rinse with water to remove

Stop use and ask a doctor if

- rash occurs

Keep out of reach of children.

If swallowed, get medical help or contact a Poison Control Center right away.

Directions

- Apply liberally 15 minutes before sun exposure
- Reapply at least every 2 hours
- Use a water-resistant sunscreen if swimming or sweating
- Spending time in the sun increases your risk of skin cancer and early skin aging. To decrease this risk, regularly use a sunscreen with a Broad Spectrum SPF value of 15 or higher and other sun protection measures including: Sun Protection Measures.
  - Limit time in the sun, especially from 10am to 2pm
  - Wear long-sleeved shirts, pants, hats, and sunglasses
  Children under 6 months: ask a doctor

Other information

Protect the product in this container from excessive heat and direct sun.

Inactive ingredients

Water/Aqua, Caprylic/Capric Triglyceride, Isoamyl Laurate, Coconut Alkanes, Glycerin, Polyglyceryl-3 Polyricinoleate, Silica, Glyceryl Caprylate, Lecithin, Rose (Rosa Damascena) Flower Extract, Algae, Aloe (Aloe Barbadensis) Leaf Juice, Isostearic Acid, Polyhydroxystearic Acid, Sunflower (Helianthus Annuus) Seed Oil, Sweet Iris (Iris Pallida) Leaf Cell Extract, Polyglyceryl-6 Polyricinoleate, Sodium Chloride, Coco-Caprylate/Caprate, Kukui (Aleurites Moluccanus) Seed Oil, Pumpkin (Cucurbita Pepo) Seed Oil, Squalane, Xanthan Gum, Tamanu (Calophyllum Inophylum) Seed Oil, Pomegranate (Punica Granatum) Extract, Chaparral (Larrea Tridentata) Extract, Leuconostoc/Radish Root Ferment Filtrate, Bisabolol, Tocopherol, Sodium Hyaluronate, Citric Acid